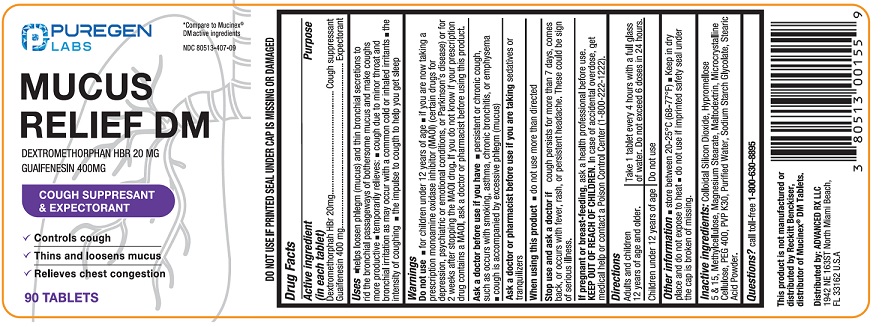 DRUG LABEL: MUCUS RELIEF DM
NDC: 80513-407 | Form: TABLET
Manufacturer: Advanced Rx LLC
Category: otc | Type: HUMAN OTC DRUG LABEL
Date: 20250101

ACTIVE INGREDIENTS: DEXTROMETHORPHAN HYDROBROMIDE 20 mg/1 1; GUAIFENESIN 400 mg/1 1
INACTIVE INGREDIENTS: SILICON DIOXIDE; HYPROMELLOSE 2910 (5 MPA.S); HYPROMELLOSE 2910 (15 MPA.S); METHYLCELLULOSE, UNSPECIFIED; MAGNESIUM STEARATE; MALTODEXTRIN; MICROCRYSTALLINE CELLULOSE; POLYETHYLENE GLYCOL 400; POVIDONE K30; WATER; SODIUM STARCH GLYCOLATE TYPE A; STEARIC ACID

MUCUS RELIEF DM

Active ingredient (in each tablet)

Dextromethorphan HBr 20 mg
Guaifenesin 400 mg

Purpose

Cough suppressant

Expectorant

Uses

- helps loosen phlegm (mucus) and thin bronchial secretions to rid the bronchial passageways of bothersome mucus and make coughs more productive
- temporarily relieves:
- cough due to minor throat and bronchial irritation as may occur with the common cold or inhaled irritants
- the intensity of coughing
- the impulse to cough to help you get to sleep

Warnings

Do not use

- for children under 12 years of age
- if you are now taking a prescription monoamine oxidase inhibitor (MAOI) (certain drugs for depression, psychiatric or emotional conditions, or Parkinson’s disease), or for 2 weeks after stopping the MAOI drug. If you do not know if your prescription drug contains a MAOI, ask a doctor or pharmacist before taking this product.

Ask a doctor before use if you have

- persistent or chronic cough such as occurs with smoking, asthma, chronic bronchitis, or emphysema
- cough is accompanied by excessive phlegm (mucus)

Ask a doctor or pharmcists before use if you are takingsedatives or tranquilizers

When using this productdo not use more than directed

Stop use and ask a doctor ifcough lasts more than 7 days, comes back, or occurs with fever, rash or persistent headache. These could be signs of a serious illness.

If pregnant or breast-feeding,ask a health professional before use.

Keep out of reach of children. In case of accidental overdose, get medical help or contact a Poison Control Center (1-800-222-1222).

Directions

- Adults and children 12 years of age and older:Take 1 tablet every 4 hours with a full glass of water. Do not exceed 6 doses in 24 hours.
- Children under 12 years of age:Do not use

Other information

- store between 20° - 25°C (68° - 77°F)
- Keep in dry place and do not expose to heat
- do not use if imprinted safety seal under the cap is broken or missing.

Inactive ingredients

Colloidal Silicon Dioxide, Hypromellose 5 & 15, Magnesium Stearate, Maltodextrin, Microcrystalline Cellulose, PEG 400, PVP K30, Purified Water, Sodium Starch Glycolate, Stearic Acid Powder.

Questions?

call toll free 1-800-630-8895

Distributed by:

ADVANCED RX LLC

1942 NE 163ST North Miami Beach,

FL 33162 U.S.A

PRINCIPAL DISPLAY PANEL

NDC 80513-407-09

*Compare to Mucine® DM active ingredients

Mucus Relief DM

Dextromethorphan HBr 20 mg

Guaifenesin 400 mg

Cough Suppresant & Expectorant

90 Tablets

*This product is not manufactured or distributed by Reckitt Benckiser, distributor of Mucinex® DM Tablets.